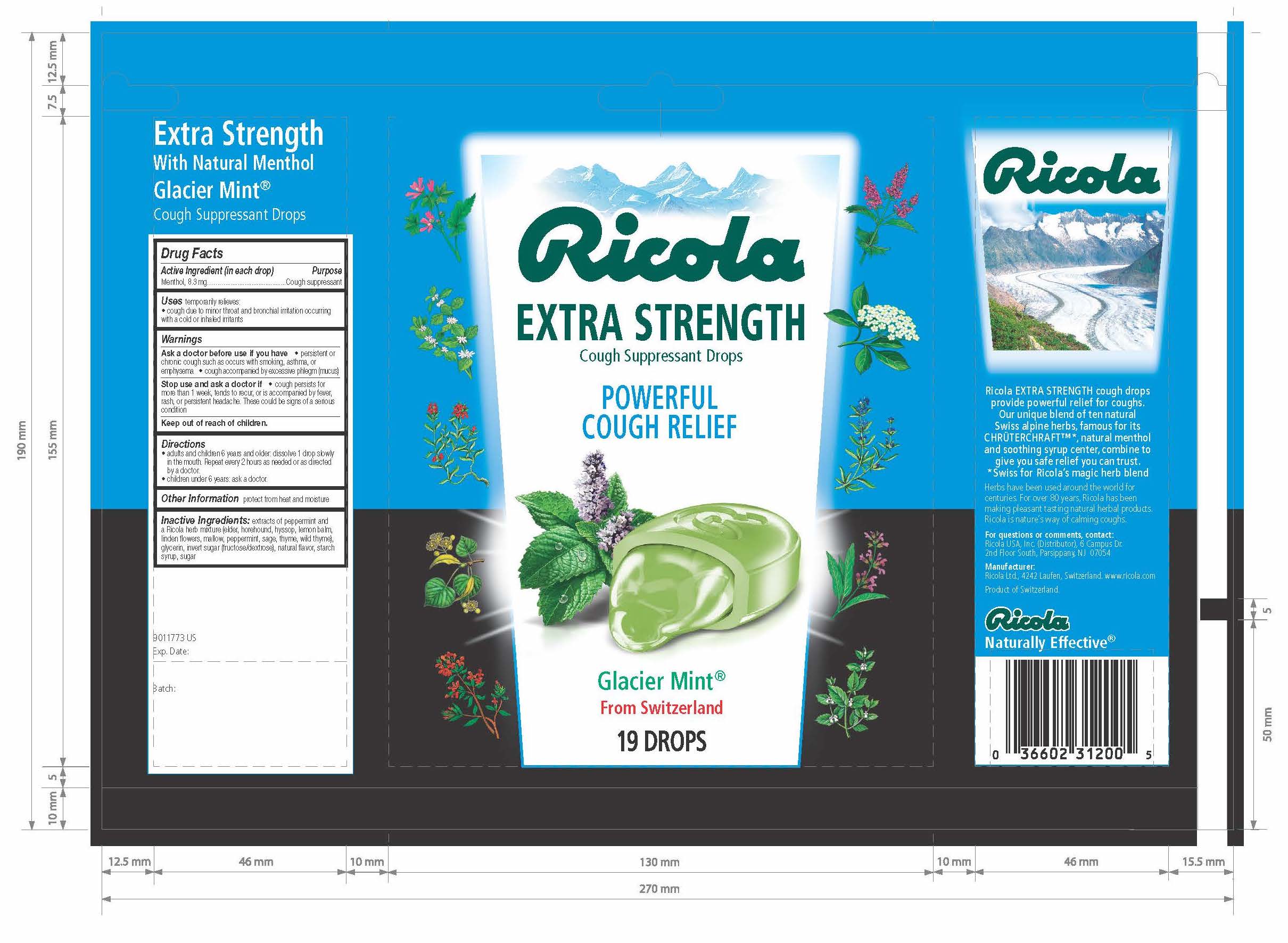 DRUG LABEL: EXTRA STRENGTH WITH NATURAL MENTHOL GLACIER MINT COUGH SUPPRESSANT
NDC: 63667-503 | Form: LOZENGE
Manufacturer: Ricola USA Inc.
Category: otc | Type: HUMAN OTC DRUG LABEL
Date: 20241210

ACTIVE INGREDIENTS: MENTHOL 8.3 mg/1 1
INACTIVE INGREDIENTS: SUCROSE; GLYCERIN; INVERT SUGAR; PEPPERMINT

EXTRA STRENGTH WITH NATURAL MENTHOL GLACIER MINT

Drug Facts

Purpose

Cough suppressant

Active Ingredient (in each drop)

Menthol, 8.3 mg

Uses

temporarily relieves:

- cough due to minor throat and bronchial irritation occurring with a cold or inhaled irritants

Ask doctor before use if you have

- persistent chronic cough such as occurs with smoking, asthma, or emphysema
- cough accompanied by excessive phlegm (mucus)

Stop use and ask a doctor if

- cough persists for more than 1 week, tends to recur, or is accompanied by fever, rash, or persistent headache. These could be signs of a serious condition

Directions

- adults and children 6 years and older: dissolve 1 drop slowly in the mouth. Repeat every 2 hours as needed or as directed by a doctor
- children under 6 years: ask a doctor

Other Information

Store in a dry place

Inactive Ingredients

extracts of peppermint and a Ricola herb mixture (elder, horehound, hyssop, lemon balm, linden flowers, mallow, peppermint, sage, thyme, wild thyme), glycerin, invert sugar (fructose/dextrose), natural flavor, starch syrup, sugar